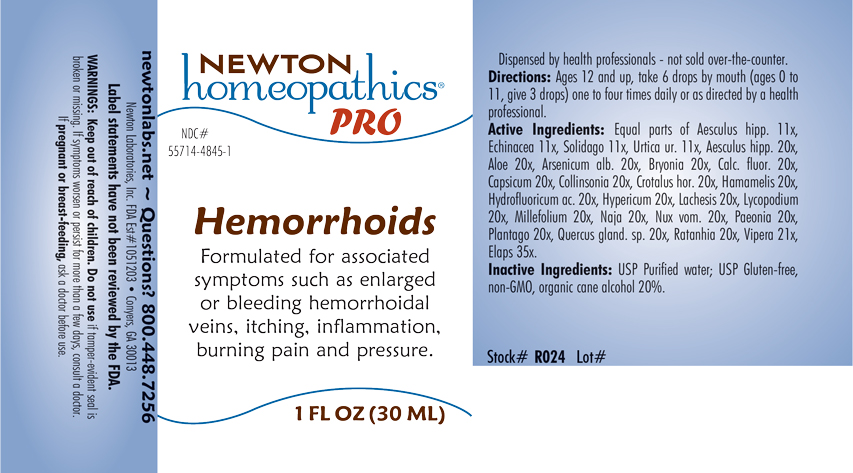 DRUG LABEL: Hemorrhoids
NDC: 55714-4845 | Form: LIQUID
Manufacturer: Newton Laboratories, Inc.
Category: homeopathic | Type: HUMAN OTC DRUG LABEL
Date: 20210712

ACTIVE INGREDIENTS: MICRURUS CORALLINUS VENOM 35 [hp_X]/1 mL; HORSE CHESTNUT 20 [hp_X]/1 mL; ALOE 20 [hp_X]/1 mL; ARSENIC TRIOXIDE 20 [hp_X]/1 mL; BRYONIA ALBA ROOT 20 [hp_X]/1 mL; CALCIUM FLUORIDE 20 [hp_X]/1 mL; CAPSICUM 20 [hp_X]/1 mL; COLLINSONIA CANADENSIS ROOT 20 [hp_X]/1 mL; CROTALUS HORRIDUS HORRIDUS VENOM 20 [hp_X]/1 mL; HAMAMELIS VIRGINIANA ROOT BARK/STEM BARK 20 [hp_X]/1 mL; HYDROFLUORIC ACID 20 [hp_X]/1 mL; HYPERICUM PERFORATUM 20 [hp_X]/1 mL; LACHESIS MUTA VENOM 20 [hp_X]/1 mL; LYCOPODIUM CLAVATUM SPORE 20 [hp_X]/1 mL; ACHILLEA MILLEFOLIUM 20 [hp_X]/1 mL; NAJA NAJA VENOM 20 [hp_X]/1 mL; STRYCHNOS NUX-VOMICA SEED 20 [hp_X]/1 mL; PAEONIA OFFICINALIS ROOT 20 [hp_X]/1 mL; PLANTAGO MAJOR 20 [hp_X]/1 mL; QUERCUS ROBUR NUT 20 [hp_X]/1 mL; KRAMERIA LAPPACEA ROOT 20 [hp_X]/1 mL; VIPERA BERUS VENOM 21 [hp_X]/1 mL; ECHINACEA, UNSPECIFIED 11 [hp_X]/1 mL; SOLIDAGO VIRGAUREA FLOWERING TOP 11 [hp_X]/1 mL; URTICA URENS 11 [hp_X]/1 mL
INACTIVE INGREDIENTS: ALCOHOL; WATER

Hemorrhoids 4845L

INDICATIONS & USAGE SECTION

Formulated for associated symptoms such as enlarged or bleeding hemorrhoidal veins, itching, inflammation, burning pain and pressure.

DOSAGE & ADMINISTRATION SECTION

Directions: Ages 12 and up, take 6 drops by mouth (ages 0 to 11, give 3 drops) one to four times daily or as directed by a health professional.

OTC - ACTIVE INGREDIENT SECTION

Equal parts of Aesculus hippocastanum 11x, Echinacea 11x, Solidago virgaurea 11x, Urtica urens 11x, Aesculus hippocastanum 20x, Aloe 20x, Arsenicum album 20x, Bryonia 20x, Calcarea fluorica 20x, Capsicum annuum 20x, Collinsonia canadensis 20x, Crotalus horridus 20x, Hamamelis virginiana 20x, Hydrofluoricum acidum 20x, Hypericum perforatum 20x, Lachesis mutus 20x, Lycopodium clavatum 20x, Millefolium 20x, Naja tripudians 20x, Nux vomica 20x, Paeonia officinalis 20x, Plantago major 20x, Quercus glandium spiritus 20x, Ratanhia 20x, Vipera berus 20x, Elaps corallinus 35x.

OTC - PURPOSE SECTION

Formulated for associated symptoms such as enlarged or bleeding hemorrhoidal veins, itching, inflammation, burning pain and pressure.

INACTIVE INGREDIENT SECTION

Inactive Ingredients: USP Purified Water; USP Gluten-free, non-GMO, organic cane alcohol 20%.

QUESTIONS SECTION

newtonlabs.net – Questions? 800.448.7256

Newton Laboratories, Inc. FDA Est # 1051203 - Conyers, GA 30013

WARNINGS SECTION

WARNINGS: Keep out of reach of children. Do not use if tamper-evident seal is broken or missing. If symptoms worsen or persist for more than a few days, consult a doctor. If pregnant or breast-feeding, ask a doctor before use.

OTC - PREGNANCY OR BREAST FEEDING SECTION

If pregnant or breast-feeding, ask a doctor before use.

OTC - KEEP OUT OF REACH OF CHILDREN SECTION

Keep out of reach of children